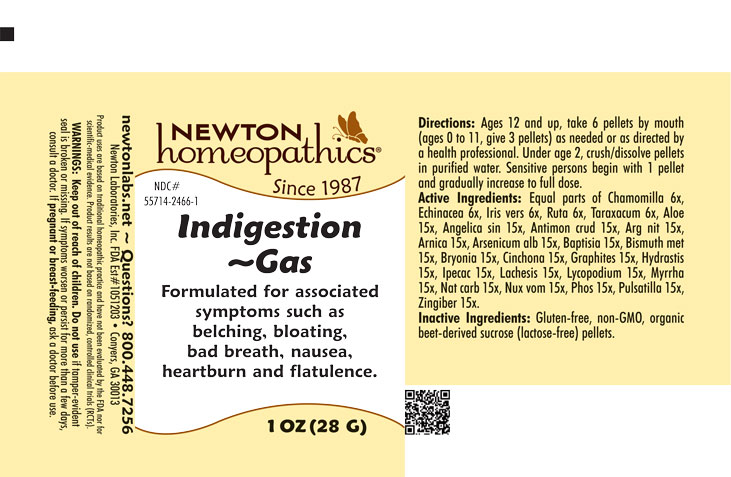 DRUG LABEL: Indigestion-Gas
NDC: 55714-2466 | Form: PELLET
Manufacturer: Newton Laboratories, Inc.
Category: homeopathic | Type: HUMAN OTC DRUG LABEL
Date: 20250820

ACTIVE INGREDIENTS: MATRICARIA CHAMOMILLA 6 [hp_X]/1 g; SODIUM CARBONATE 15 [hp_X]/1 g; IRIS VERSICOLOR ROOT 6 [hp_X]/1 g; RUTA GRAVEOLENS FLOWERING TOP 6 [hp_X]/1 g; TARAXACUM OFFICINALE 6 [hp_X]/1 g; ALOE 15 [hp_X]/1 g; ANGELICA SINENSIS ROOT 15 [hp_X]/1 g; ANTIMONY TRISULFIDE 15 [hp_X]/1 g; SILVER NITRATE 15 [hp_X]/1 g; ARNICA MONTANA 15 [hp_X]/1 g; ARSENIC TRIOXIDE 15 [hp_X]/1 g; BAPTISIA TINCTORIA 15 [hp_X]/1 g; BISMUTH 15 [hp_X]/1 g; BRYONIA ALBA ROOT 15 [hp_X]/1 g; CINCHONA OFFICINALIS BARK 15 [hp_X]/1 g; GRAPHITE 15 [hp_X]/1 g; GOLDENSEAL 15 [hp_X]/1 g; IPECAC 15 [hp_X]/1 g; LACHESIS MUTA VENOM 15 [hp_X]/1 g; LYCOPODIUM CLAVATUM SPORE 15 [hp_X]/1 g; MYRRH 15 [hp_X]/1 g; PHOSPHORUS 15 [hp_X]/1 g; ANEMONE PULSATILLA 15 [hp_X]/1 g; GINGER 15 [hp_X]/1 g; STRYCHNOS NUX-VOMICA SEED 15 [hp_X]/1 g; ECHINACEA, UNSPECIFIED 6 [hp_X]/1 g
INACTIVE INGREDIENTS: SUCROSE

Indigestion 2466P

INDICATIONS & USAGE SECTION

Formulated for associated symptoms such as belching, bloating, bad breath, nausea, heartburn and flatulence.

DOSAGE & ADMINISTRATION SECTION

Directions: Ages 12 and up, take 6 pellets by mouth (ages 0 to 11, give 3 pellets) as needed or as directed by a health professional. Sensitive persons begin with 1 pellet and gradually increase to full dose.

OTC - ACTIVE INGREDIENT SECTION

Equal parts of Chamomilla 6x, Echinacea 6x, Iris versicolor 6x, Ruta graveolens 6x, Taraxacum officinale 6x, Aloe 15x, Angelica sinensis radix 15x, Antimonium crudum 15x, Argentum nitricum 15x, Arnica montana 15x, Arsenicum album 15x, Baptisia tinctoria 15x, Bismuthum metallicum 15x, Bryonia 15x, Cinchona officinalis 15x, Graphites 15x, Hydrastis canadensis 15x, Ipecacuanha 15x, Lachesis mutus 15x, Lycopodium clavatum 15x, Myrrha 15x, Natrum carbonicum 15x, Nux vomica 15x, Phosphorus 15x, Pulsatilla 15x, Zingiber officinale 15x.

OTC - PURPOSE SECTION

Formulated for associated symptoms such as belching, bloating, bad breath, nausea, heartburn and flatulence.

INACTIVE INGREDIENT SECTION

Inactive Ingredients: USP Purified Water; USP Gluten-free, non-GMO, organic cane alcohol 20%.

QUESTIONS SECTION

newtonlabs.net - Questions? 800.448.7256

Newton Laboratories, Inc. FDA Est # 1051203 Conyers, GA 30013

WARNINGS SECTION

WARNINGS: Keep out of reach of children. Do not use if tamper-evident seal is broken or missing. If symptoms worsen or persist for more than a few days, consult a doctor. If pregnant or breast-feeding, ask a doctor before use.

OTC - PREGNANCY OR BREAST FEEDING SECTION

If pregnant or breast-feeding, ask a doctor before use.

OTC - KEEP OUT OF REACH OF CHILDREN SECTION

Keep out of reach of children.